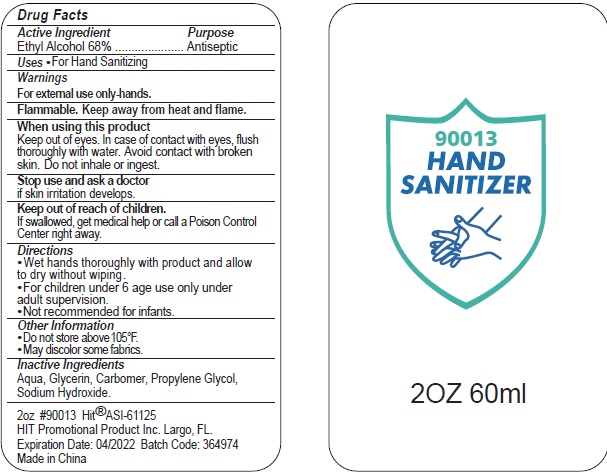 DRUG LABEL: 90013 Hand Sanitizer
NDC: 74274-009 | Form: SOLUTION
Manufacturer: Huizhou Bliss Commodity Co., Ltd
Category: otc | Type: HUMAN OTC DRUG LABEL
Date: 20200418

ACTIVE INGREDIENTS: ALCOHOL 68 mL/100 mL
INACTIVE INGREDIENTS: WATER; CARBOMER INTERPOLYMER TYPE A (ALLYL SUCROSE CROSSLINKED); GLYCERIN; PROPYLENE GLYCOL; SODIUM HYDROXIDE

Active ingredient

Ethyl Alcohol 68%

Purpose

Antiseptic

Use

For Hand Sanitizing

KEEP OUT OF REACH OF CHILDREN

if swallowed, get medical help or contact a Poison Control Center right away.

warnings:

Flamable, keep away from heat and flame.

For external use only-hands.

When using this product

Keep out of eyes. In case of contact with eyes, Flush thoroughly with water. Avoid contact wieh broken skin. Do not inhale or ingest.

Stop use and ask a doctor if skin irritation develops.

Other Information

- Do not store above 105℉
- May discolor some fabrics.

Directions

- Wet hands thoroughly with product and allow to dry without wiping.
- For children under 6 age only under adult supervision.
- Not recommended for infants.

Inactive ingredients

Aqua, glycerin, carbomer, propyene glycol, sodium hydroxide